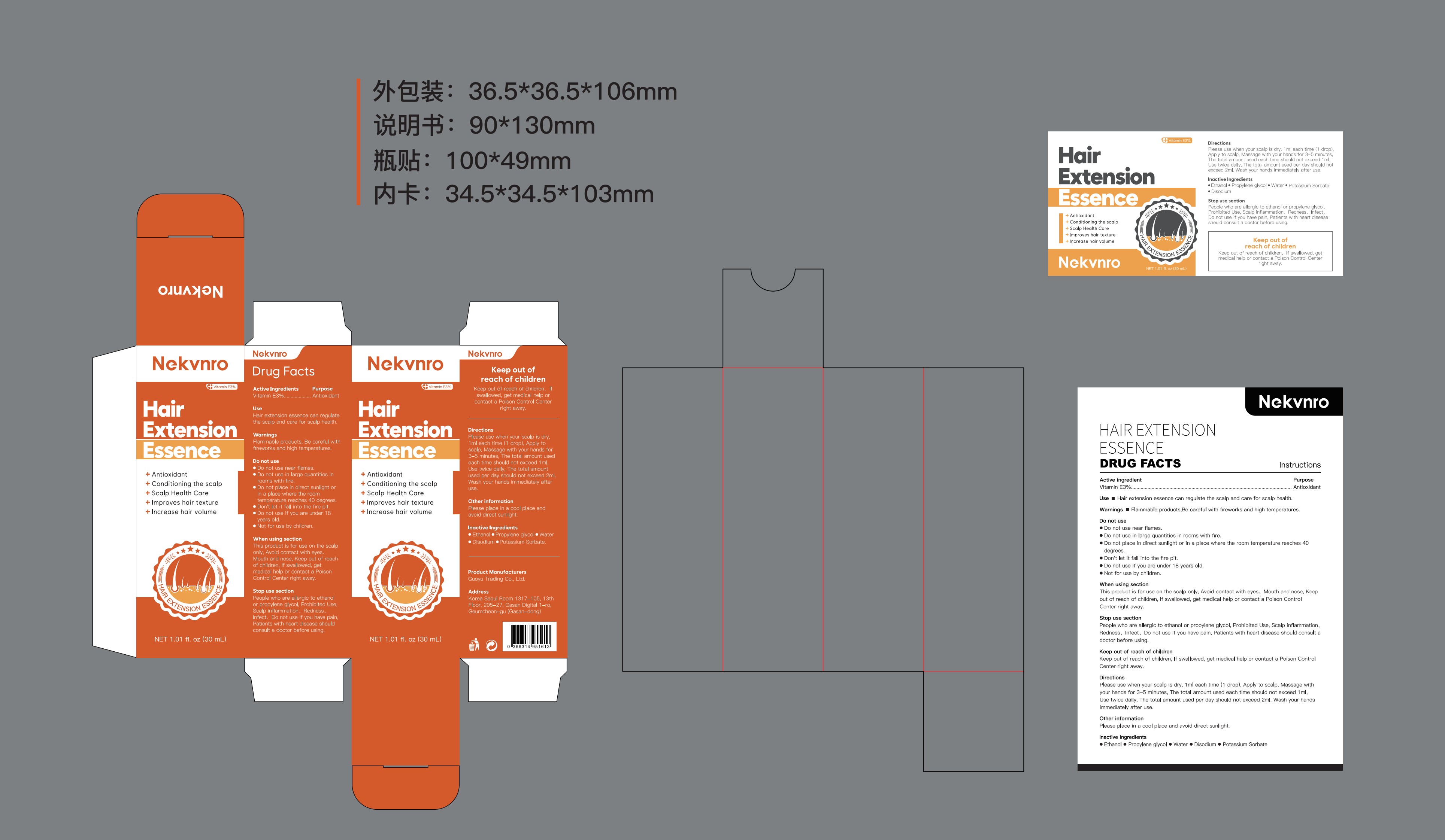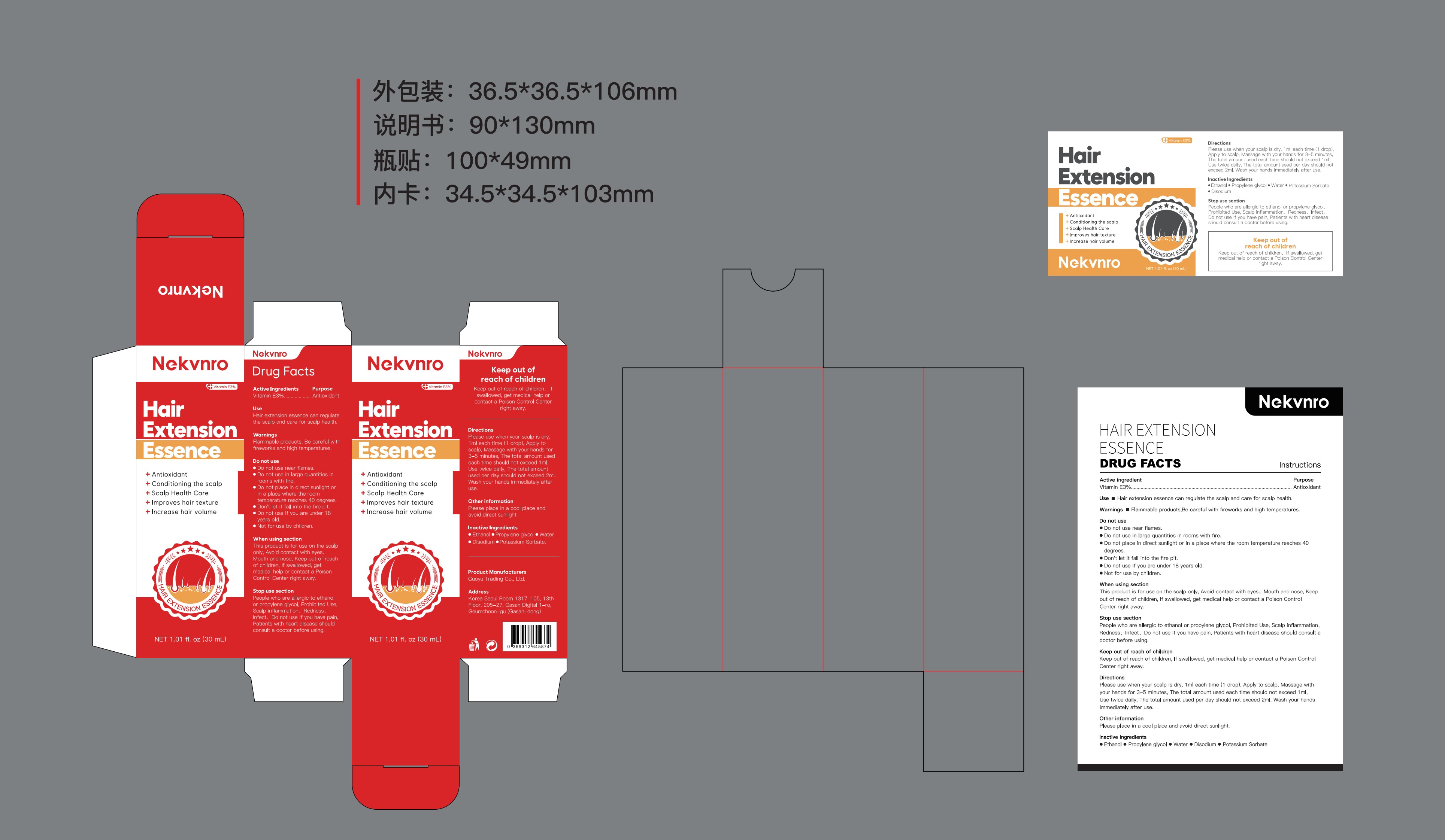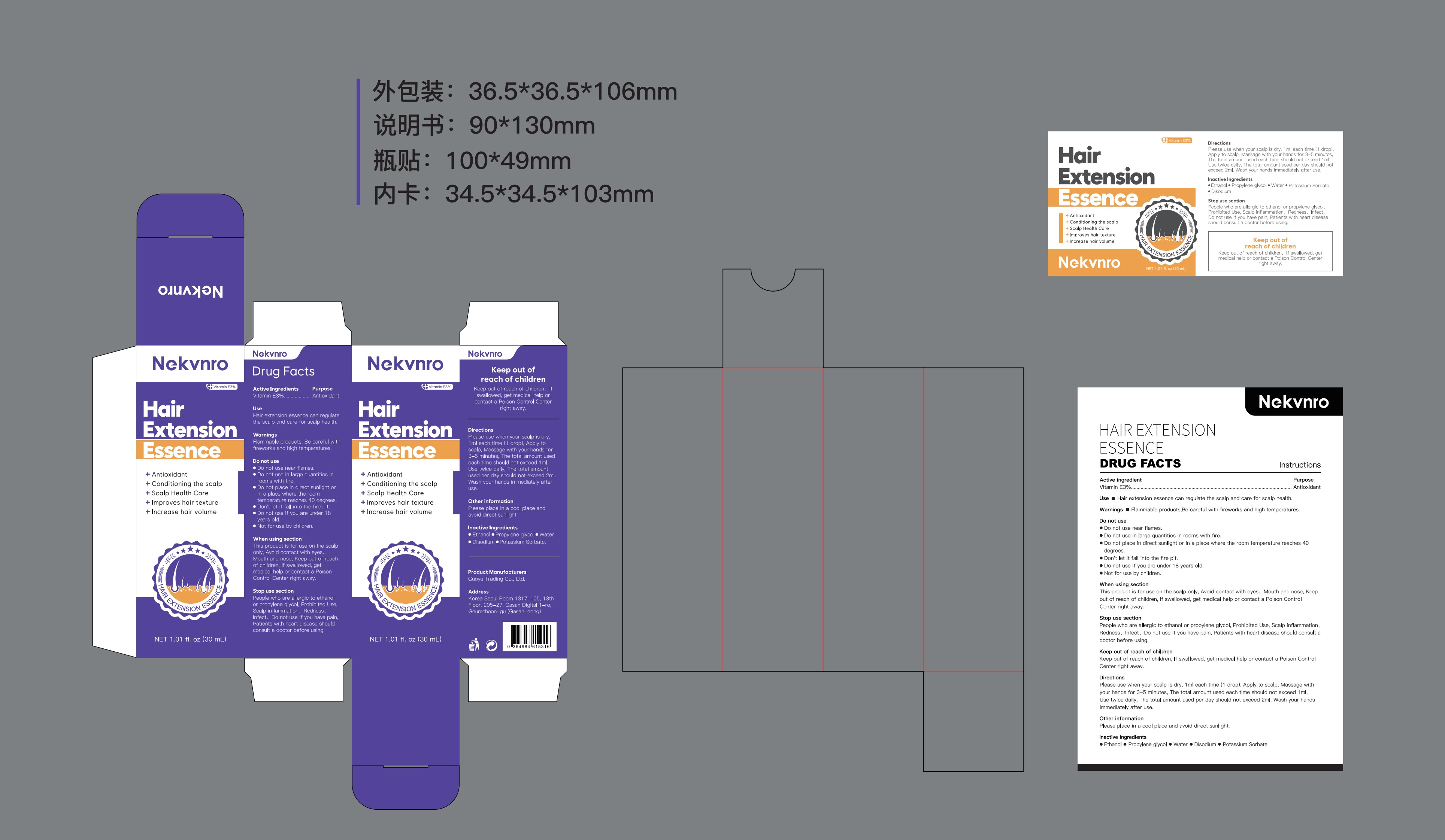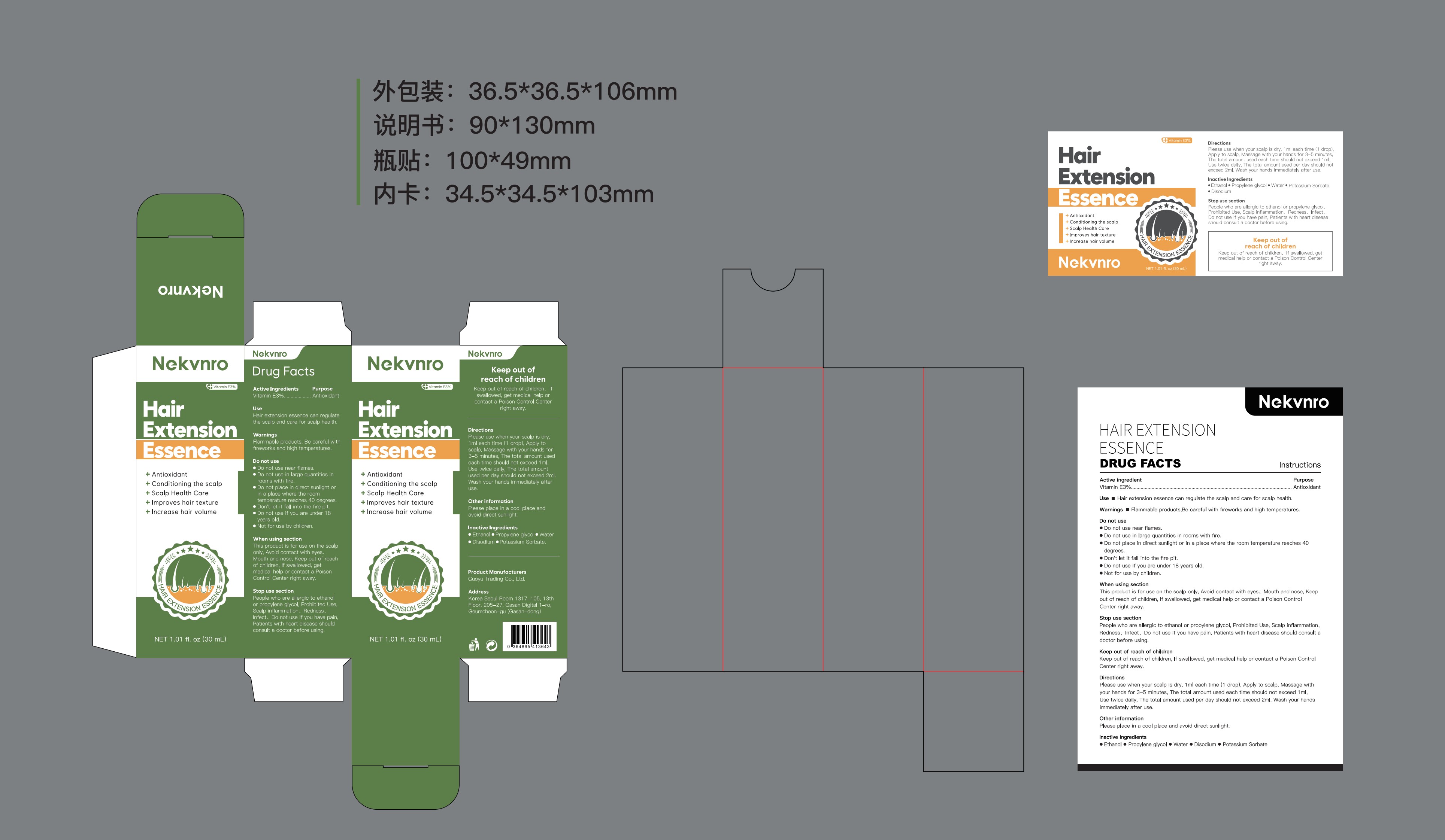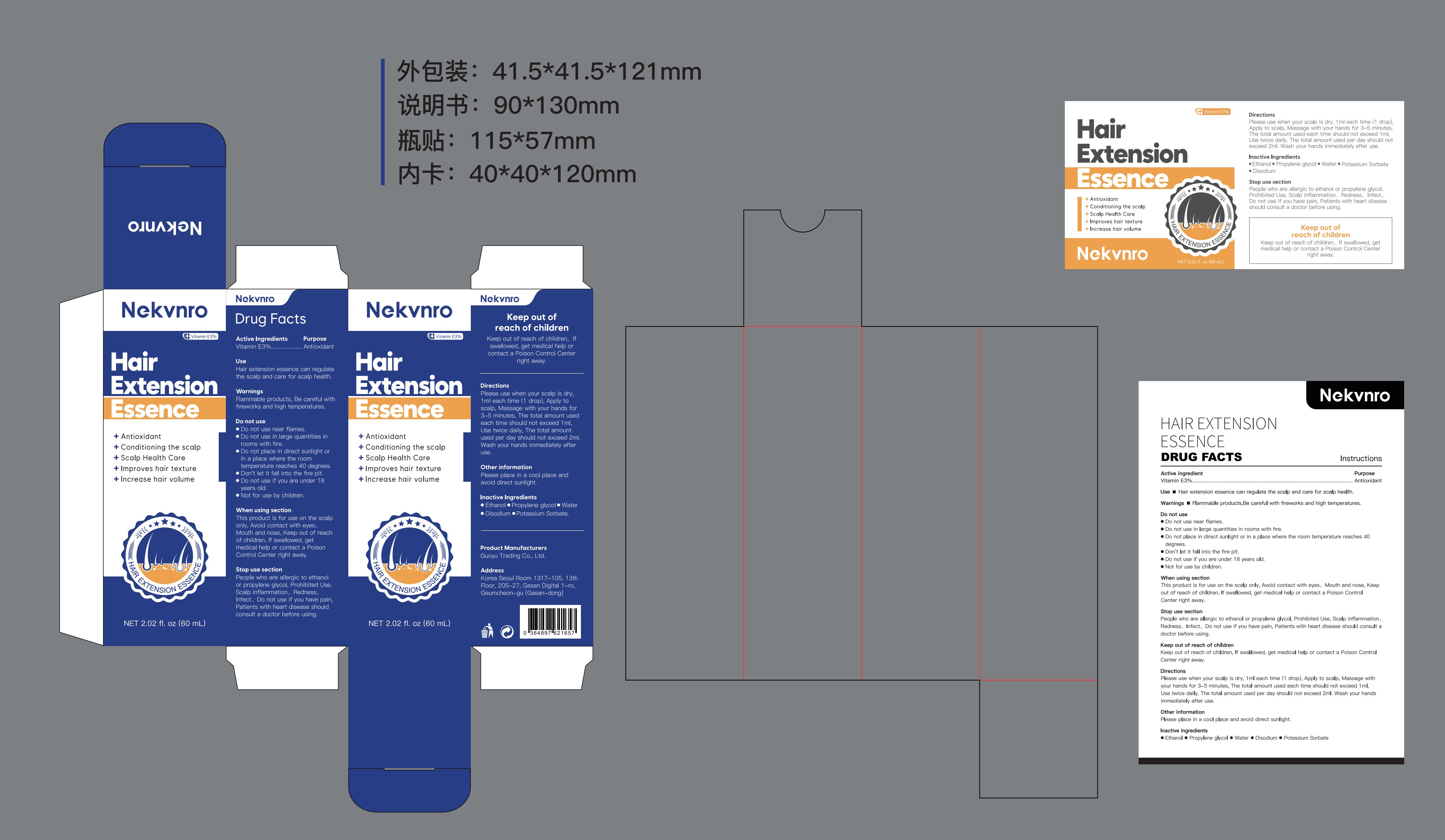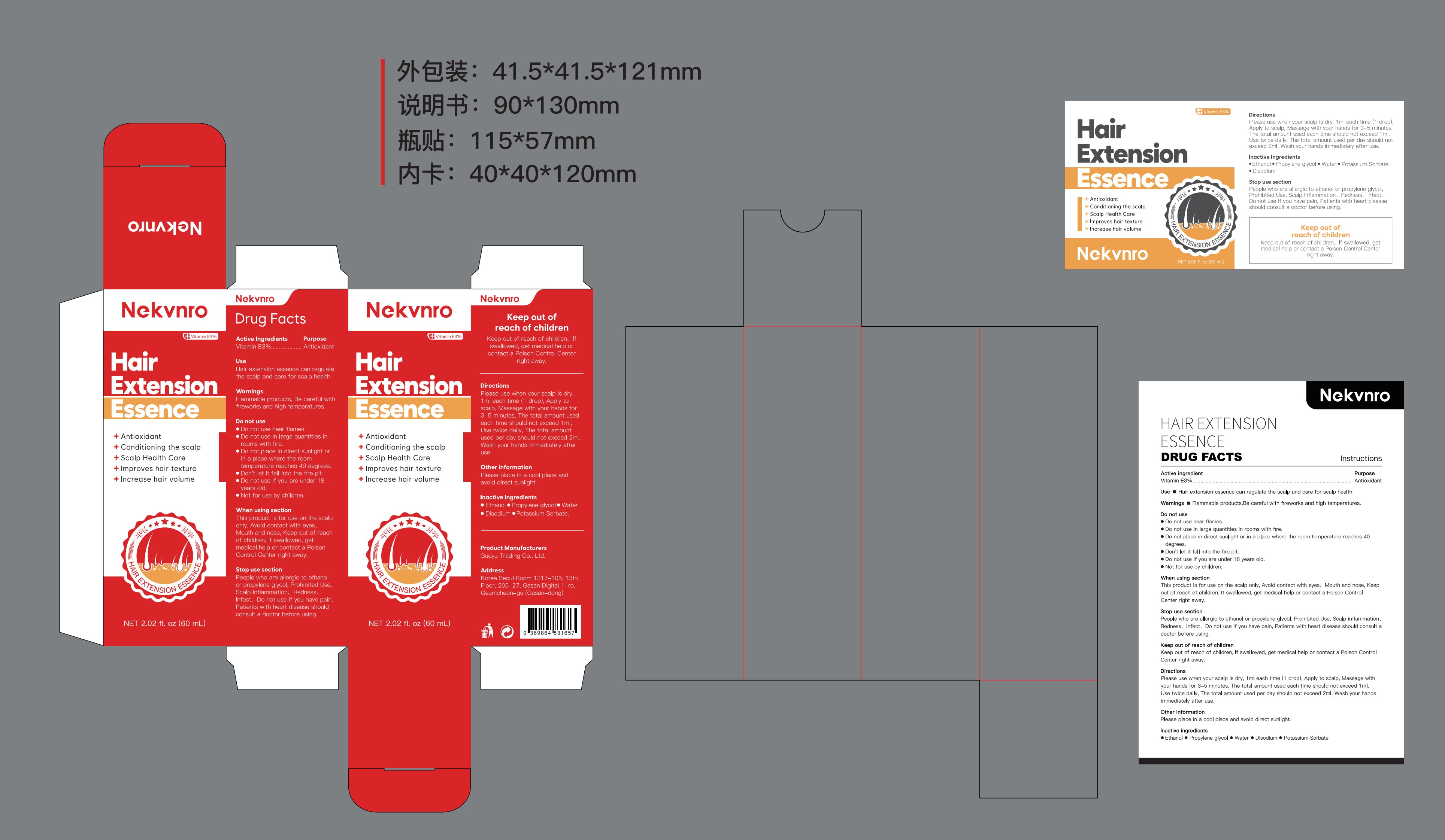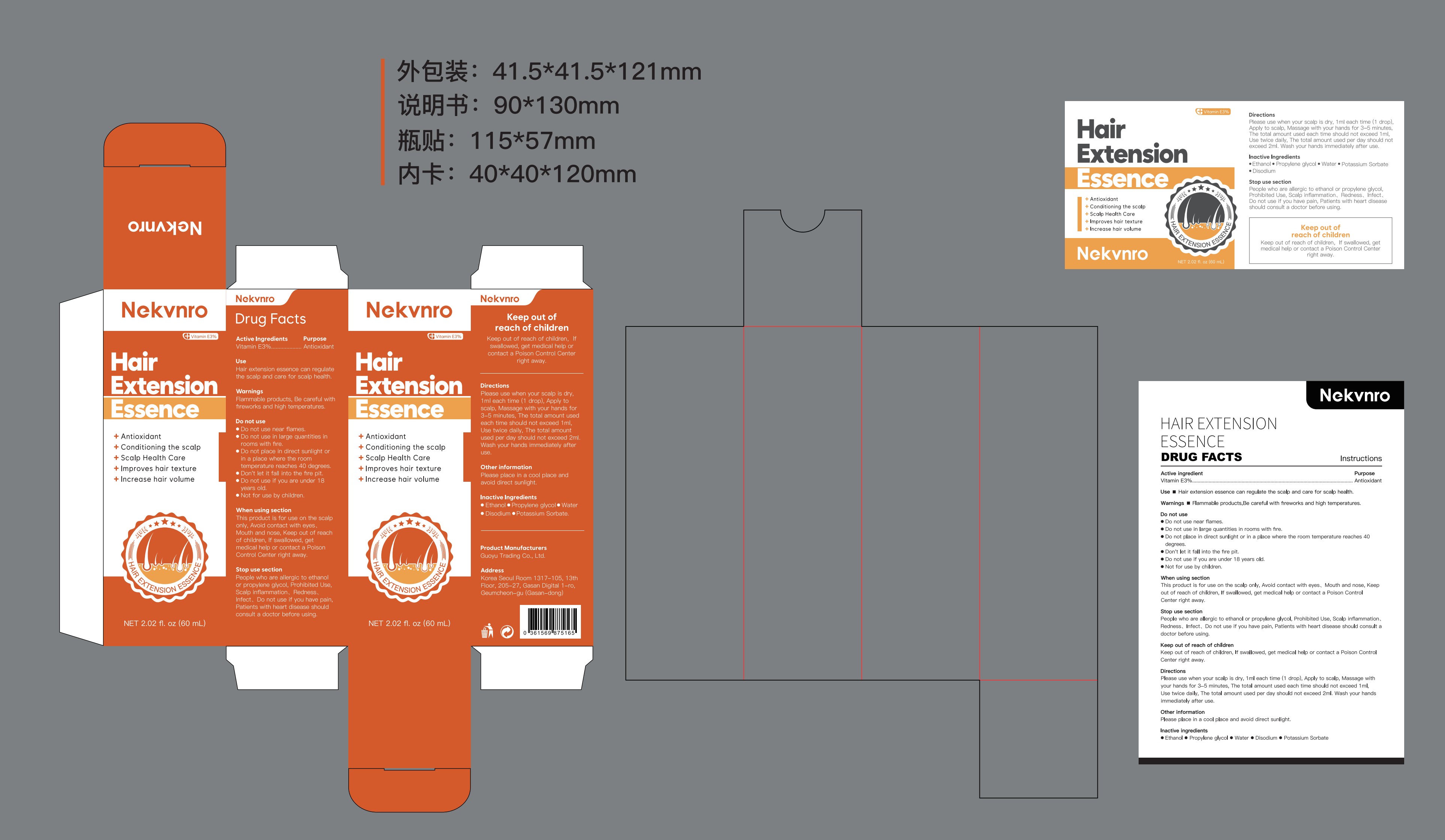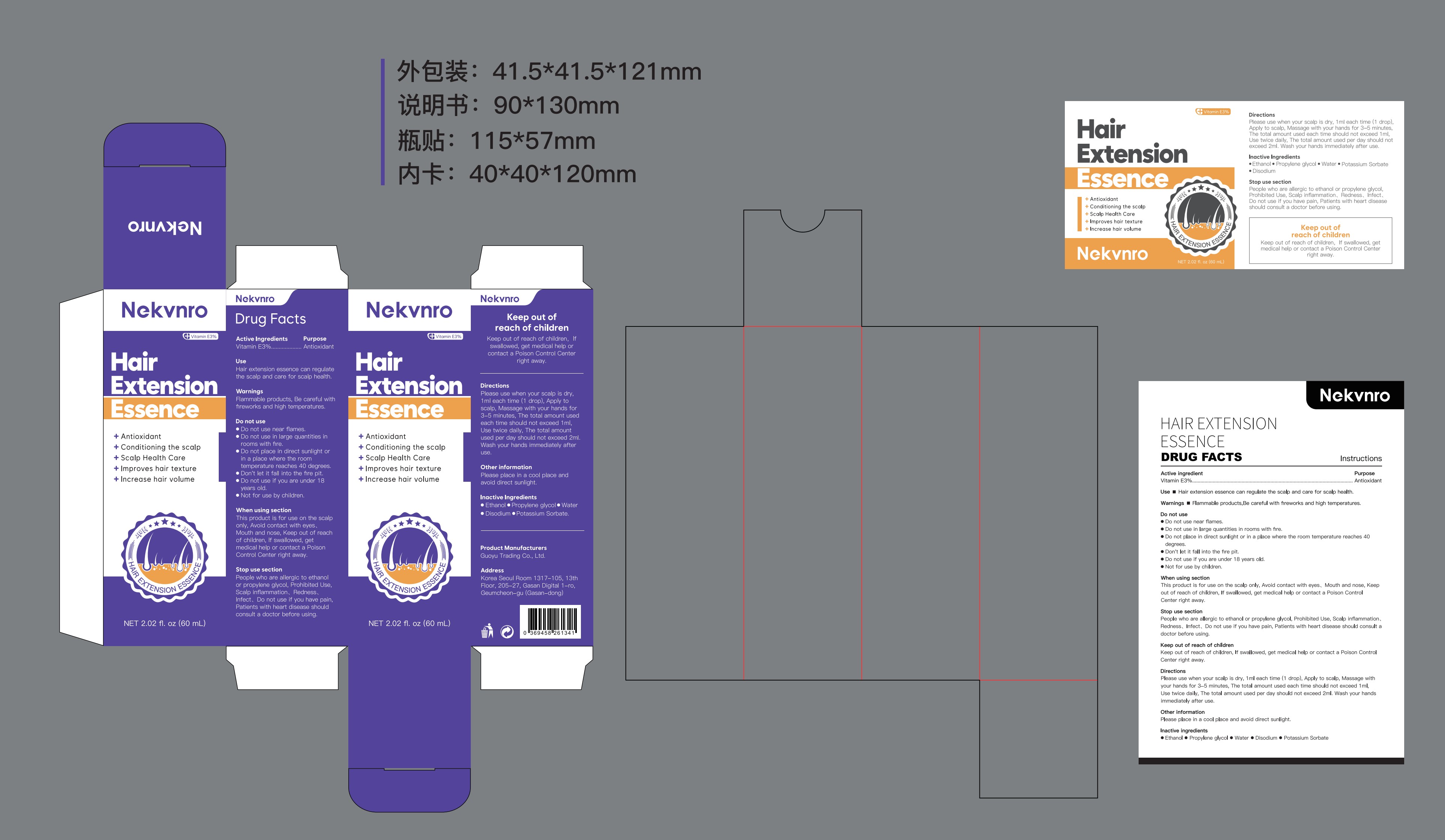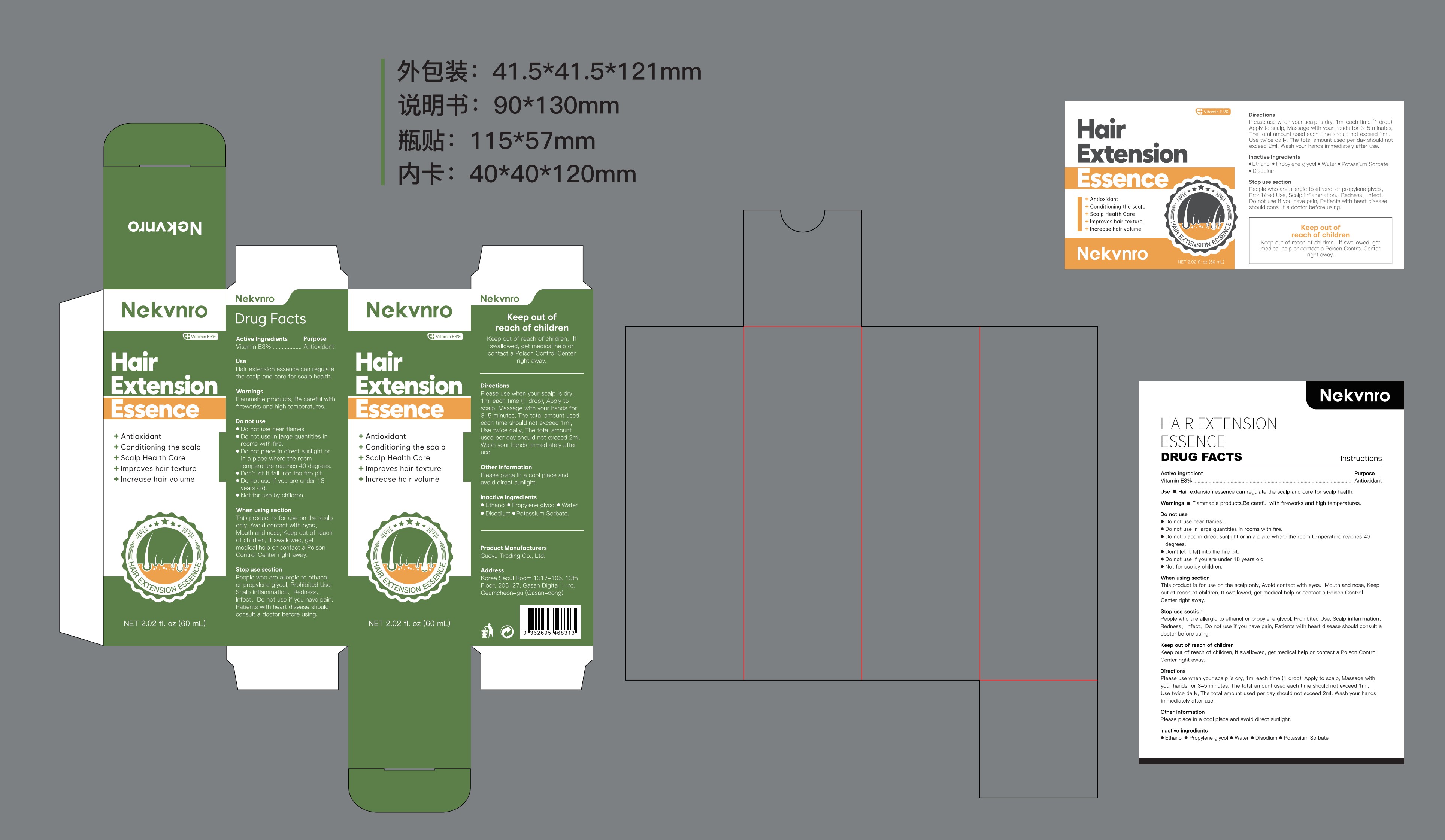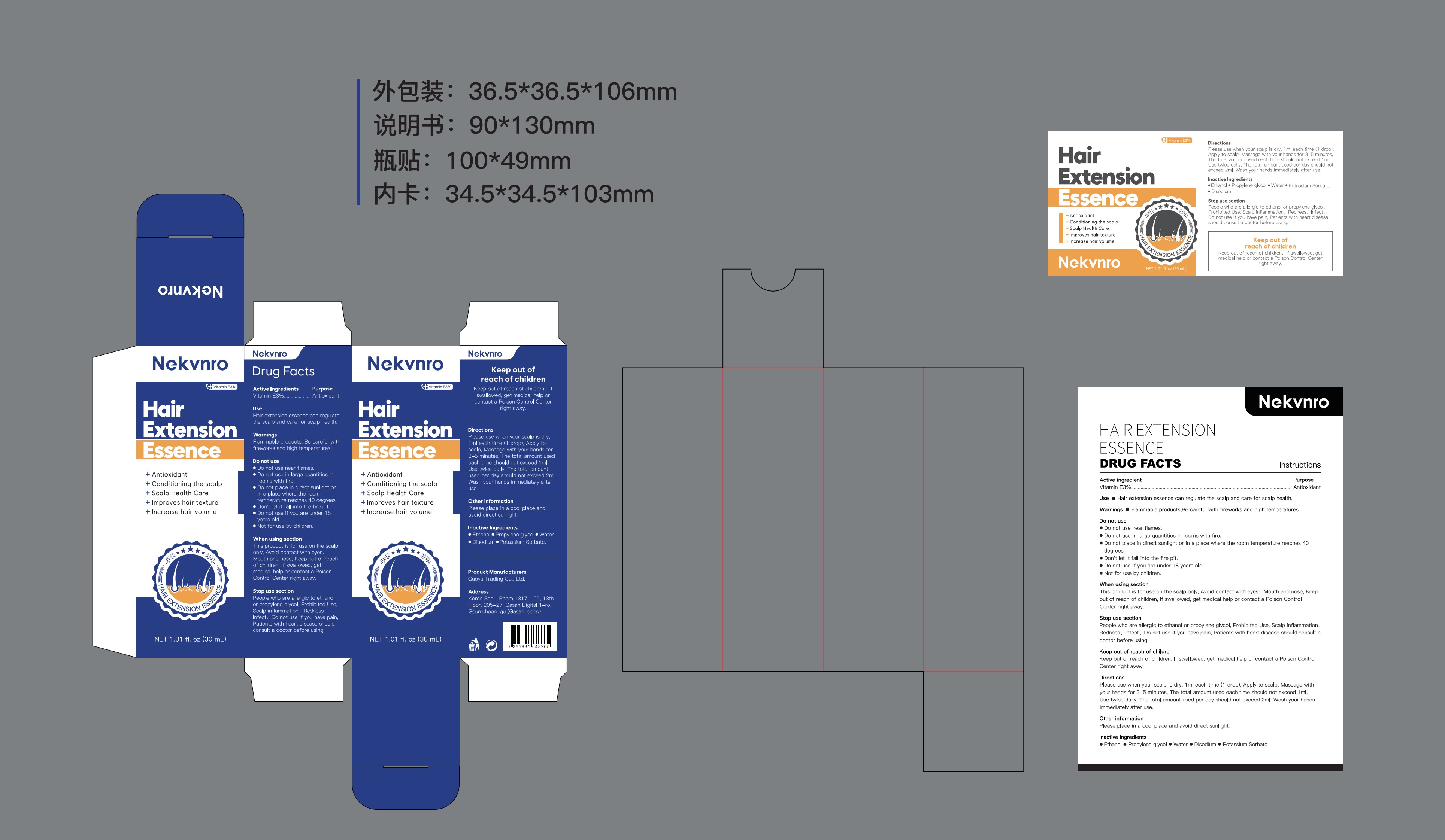 DRUG LABEL: NEKVNRO Hair Extension Essence
NDC: 84844-012 | Form: LIQUID
Manufacturer: Guoyu Trading Co., Ltd.
Category: otc | Type: HUMAN OTC DRUG LABEL
Date: 20241106

ACTIVE INGREDIENTS: .ALPHA.-TOCOPHEROL 3 g/100 mL
INACTIVE INGREDIENTS: ALCOHOL; PROPYLENE GLYCOL; WATER; EDETATE DISODIUM; POTASSIUM SORBATE

84844-012

Active Ingredient

Vitamin E 3%

Purpose

Antioxidant

Use

Hair extension essence can regulate the scalp and care for scalp health

Warnings

Flammable products,Be careful with fireworks and high temperatures

Do not use near flames,Do not use in large quantities in rooms with fire,Do not place in direct sunlight or in a place where the room temperature reaches 40 degrees,Don't let it fall into the fire pit.Do not use if you are under 18 years old,Not for use by children.

When Using

This product is for use on the scalp only,Avoid contact with eyes、Mouth and nose，Keep out of reach of children，If swallowed, get medical help or contact a Poison Control Center right away.

Stop Use

People who are allergic to ethanol or propylene glycol,Prohibited Use,Scalp inflammation、Redness、Infect、Do not use if you have pain,Patients with heart disease should consult a doctor before using.

Ask Doctor

People who are allergic to ethanol or propylene glycol,Prohibited Use,Scalp inflammation、Redness、Infect、Do not use if you have pain,Patients with heart disease should consult a doctor before using.

Keep Oot Of Reach Of Children

Keep out of reach of children，If swallowed, get medical help or contact a Poison Control Center right away.

Directions

Please use when your scalp is dry,1ml each time（1 drop）,Apply to scalp,Massage with your hands for 3-5 minutes,The total amount used each time should not exceed 1ml,Use twice daily,The total amount used per day should not exceed 2ml.Wash your hands immediately after use.

Other information

Please place in a cool place and avoid direct sunlight

Inactive ingredients

Ethanol,Propylene glycol,water,Disodium,Potassium Sorbate